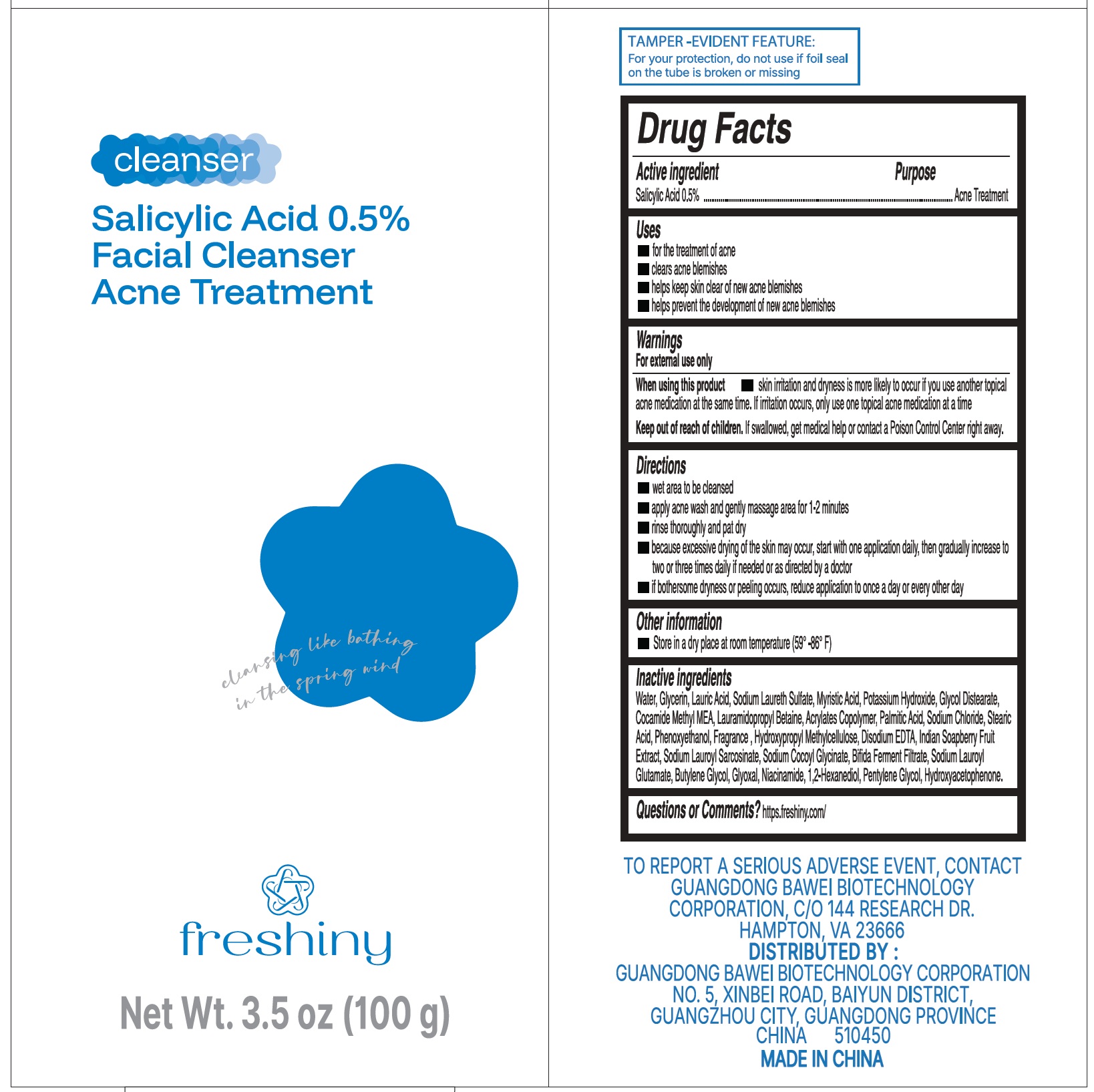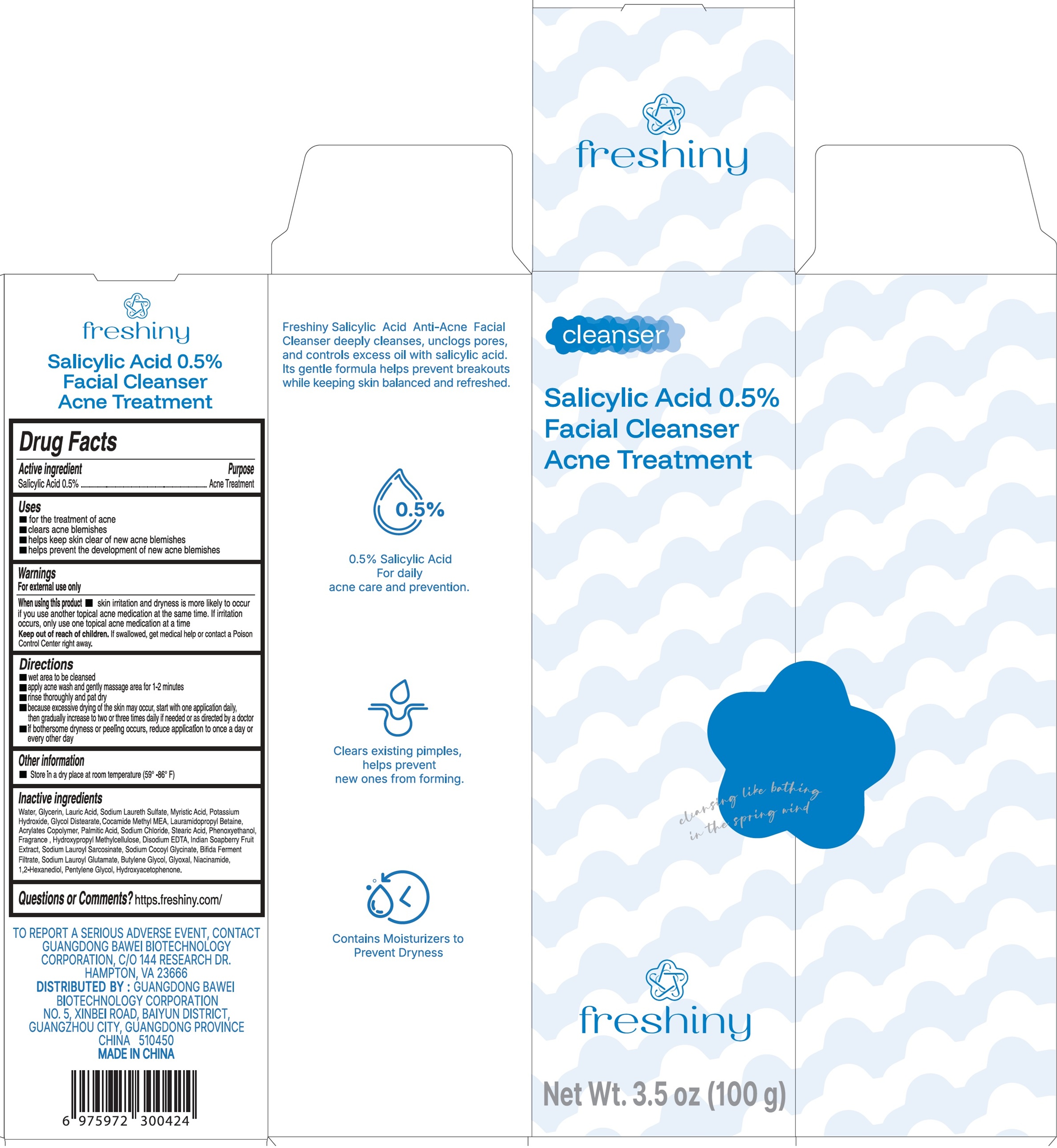 DRUG LABEL: Freshiny Facial Cleanser Acne Treatment
NDC: 84544-001 | Form: EMULSION
Manufacturer: Guangdong Bawei Biotechnology Corporation
Category: otc | Type: HUMAN OTC DRUG LABEL
Date: 20250624

ACTIVE INGREDIENTS: SALICYLIC ACID 5 mg/1 g
INACTIVE INGREDIENTS: WATER; GLYCERIN; LAURIC ACID; SODIUM LAURETH SULFATE; MYRISTIC ACID; POTASSIUM HYDROXIDE; GLYCOL DISTEARATE; COCOYL METHYL MONOETHANOLAMINE; LAURAMIDOPROPYL BETAINE; PALMITIC ACID; SODIUM CHLORIDE; STEARIC ACID; PHENOXYETHANOL; HYPROMELLOSE, UNSPECIFIED; EDETATE DISODIUM; SODIUM LAUROYL SARCOSINATE; SODIUM COCOYL GLYCINATE; SODIUM LAUROYL GLUTAMATE; BUTYLENE GLYCOL; GLYOXAL; NIACINAMIDE; 1,2-HEXANEDIOL; PENTYLENE GLYCOL; HYDROXYACETOPHENONE

Freshiny Facial Cleanser Acne Treatment

Active ingredient

Salicylic Acid 0.5%

Purpose

Acne Treatment

Uses

- for the treatment of acne
- clears acne blemishes
- helps keep skin clear of new acne blemishes
- helps prevent the development of new acne blemishes

Warnings

For external use only

When using this product

- skin irritation and dryness is more likely to occur if you use another topical acne medication at the same time. If irritation occurs, only use one topical acne medication at a time

Keep out of reach of children.

If swallowed, get medical help or contact a Poison Control Center right away.

Directions

- wet area to be cleansed
- apply acne wash and gently massage area for 1-2 minutes
- rinse thoroughly and pat dry
- because excessive drying of the skin may occur, start with one application daily, then gradually increase to two or three times daily if needed or as directed by a doctor
- if bothersome dryness or peeling occurs, reduce application to once a day or every other day

Other information

- Store in a dry place at room temperature (59°-86°F)

Inactive ingredients

Water, Glycerin, Lauric Acid, Sodium Laureth Sulfate, Myristic Acid, Potassium Hydroxide, Glycol Distearate, Cocamide Methyl MEA, Lauramidoprppyl Betaine, Acrylates Copolymer, Palmitic Acid, Sodium Chloride, Stearic Acid, Phenoxyethanol, Fragrance, Hydroxypropyl Methylcelluolose, Disodium EDTA, Indian Soapberry Fruit Extract, Sodium Lauroyl Sarcosinate, Sodium Cocoyl Glycinate, Bifida Ferment Filtrate, Sodium Lauroyl Glutamate, Butylene Glycol, Glyoxal, Niacinamide, 1,2-Hexanediol, Pentylene Glycol, Hydroxyacetophenone.

Questions or Comments?

https.freshiny.com/